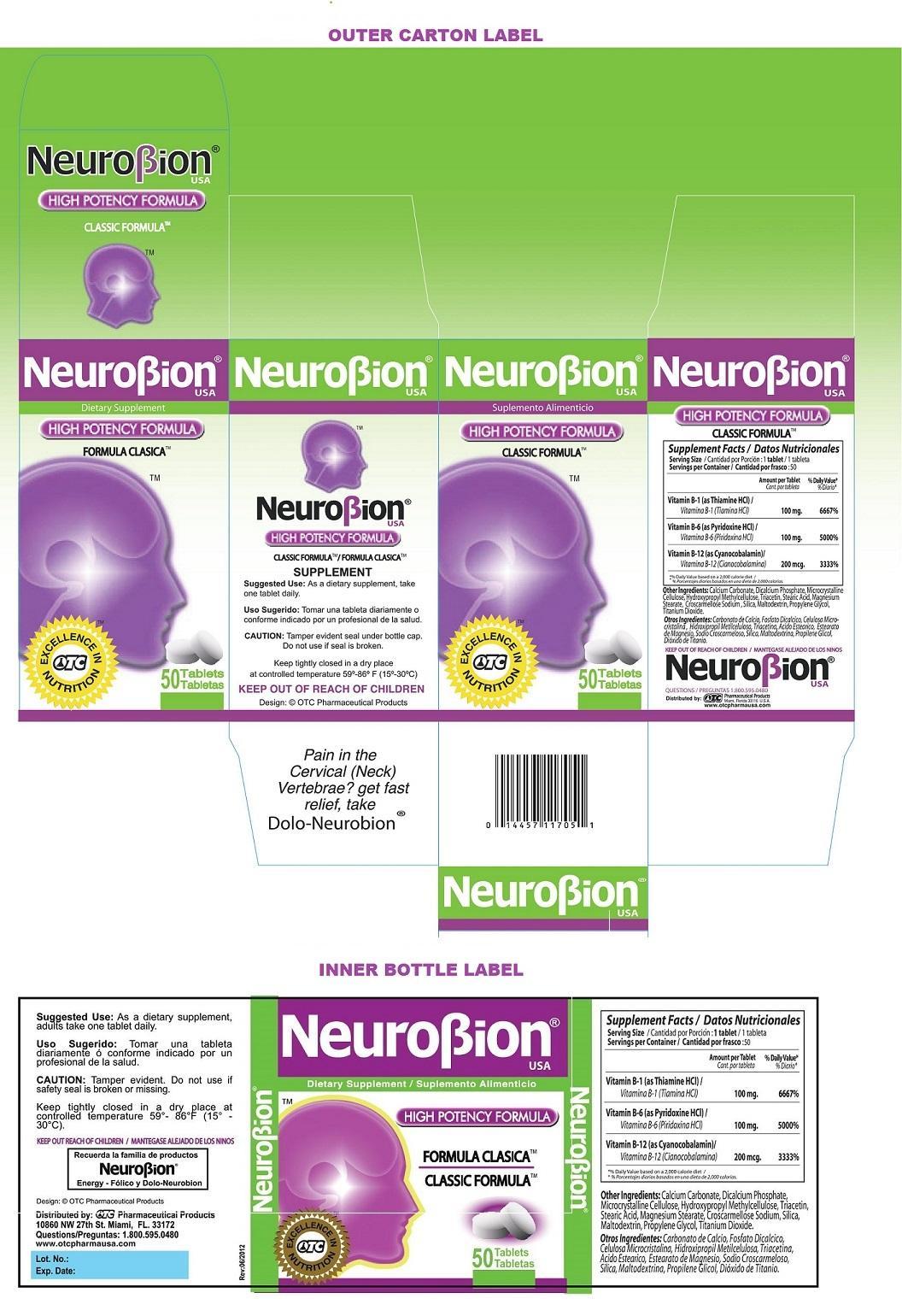 DRUG LABEL: NeuroBion
NDC: 55959-117 | Form: TABLET
Manufacturer: BENARD INDUSTRIES INC
Category: other | Type: DIETARY SUPPLEMENT
Date: 20151030

ACTIVE INGREDIENTS: THIAMINE HYDROCHLORIDE 100 mg/1 1; PYRIDOXINE HYDROCHLORIDE 100 mg/1 1; CYANOCOBALAMIN 200 ug/1 1
INACTIVE INGREDIENTS: CALCIUM CARBONATE; CALCIUM PHOSPHATE, DIBASIC, ANHYDROUS; CELLULOSE, MICROCRYSTALLINE; HYPROMELLOSE 2910 (15 MPA.S); TRIACETIN; STEARIC ACID; MAGNESIUM STEARATE; CROSCARMELLOSE SODIUM; SILICON DIOXIDE; MALTODEXTRIN; PROPYLENE GLYCOL; TITANIUM DIOXIDE

NeuroBion Tablets

STATEMENT OF IDENTITY

Supplement Facts; Serving Size : 1 tablet; Servings per Container : 50
 | Amount per Tablet | % Daily Value*
Vitamin B-1 (as Thiamine HCl) | 100 mg. | 6667%
Vitamin B-6 (as Pyridoxine HCl) | 100 mg. | 5000%
Vitamin B-12 (as Cyanocobalamin) | 200 mcg. | 3333%
*% Daily value based on a 2,000 calorie diet

Other Ingredients: Calcium Carbonate, Dicalcium Phosphate, Microcrystalline Cellulose, Hydroxypropyl Methylcellulose, Triacetin, Stearic Acid, Magnesium Stearate, Croscarmellose Sodium, Silica, Maltodextrin, Propylene Glycol, Titanium Dioxide.

KEEP OUT OF REACH OF CHILDREN

PRECAUTIONS

CAUTION: Tamper evident seal under bottle cap. Do not use if seal is broken.

SAFE HANDLING WARNING

Keep tightly closed in a dry place at controlled temperature 59°-86° F (15°-30°C)

DOSAGE AND ADMINISTRATION

Suggested Use: As a dietary supplement, take one tablet daily.

HEALTH CLAIM

HIGH POTENCY FORMULA

CLASSIC FORMULATM

DIETARY SUPPLEMENT

EXCELLENCE IN NUTRITION

Design: © OTC Pharmaceutical Products

QUESTIONS 1.800.595.0480

Distributed by:

OTC Pharmaceutical Products

10860 NW 27th St. Miami, FL 33172

www.otcpharmausa.com